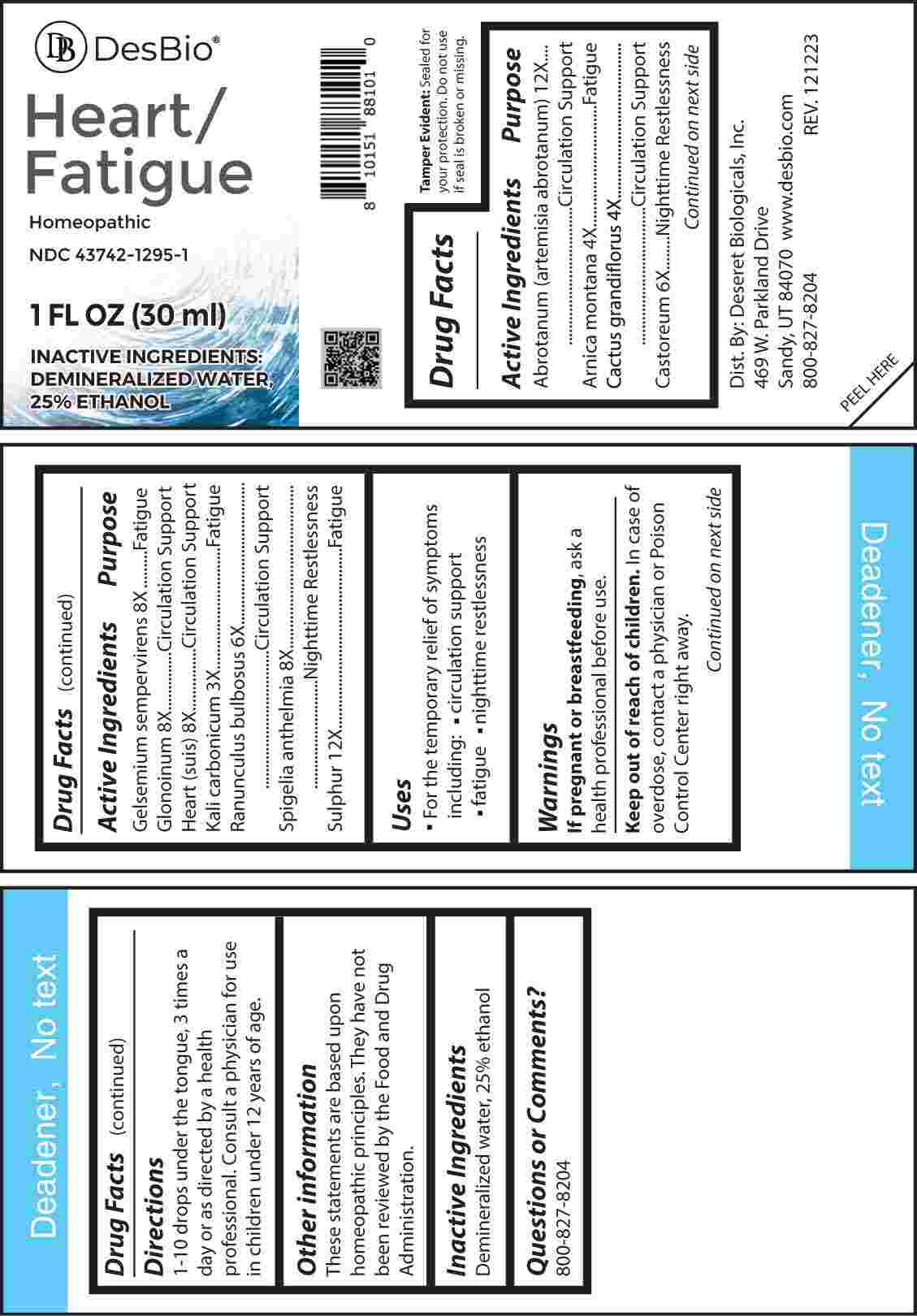 DRUG LABEL: Heart/Fatigue
NDC: 43742-1295 | Form: LIQUID
Manufacturer: Deseret Biologicals, Inc.
Category: homeopathic | Type: HUMAN OTC DRUG LABEL
Date: 20240327

ACTIVE INGREDIENTS: POTASSIUM CARBONATE 3 [hp_X]/1 mL; ARNICA MONTANA WHOLE 4 [hp_X]/1 mL; SELENICEREUS GRANDIFLORUS STEM 4 [hp_X]/1 mL; CASTOR CANADENSIS SCENT GLAND SECRETION 6 [hp_X]/1 mL; RANUNCULUS BULBOSUS 6 [hp_X]/1 mL; GELSEMIUM SEMPERVIRENS ROOT 8 [hp_X]/1 mL; NITROGLYCERIN 8 [hp_X]/1 mL; PORK HEART 8 [hp_X]/1 mL; SPIGELIA ANTHELMIA WHOLE 8 [hp_X]/1 mL; ARTEMISIA ABROTANUM FLOWERING TOP 12 [hp_X]/1 mL; SULFUR 12 [hp_X]/1 mL
INACTIVE INGREDIENTS: WATER; ALCOHOL

DRUG FACTS:

ACTIVE INGREDIENTS:

Abrotanum (Artemisia Abrotanum) 12X, Arnica Montana 4X, Cactus Grandiflorus 4X, Castoreum 6X, Gelsemium Sempervirens 8X, Glonoinum 8X, Heart (Suis) 8X, Kali Carbonicum 3X, Ranunculus Bulbosus 6X, Spigelia Anthelmia 8X, Sulphur 12X.

PURPOSE:

Abrotanum (Artemisia Abrotanum) – Circulation Support, Arnica Montana - Fatigue, Cactus Grandiflorus – Circulation Support, Castoreum – Nighttime Restlessness, Gelsemium Sempervirens - Fatigue, Glonoinum – Circulation Support, Heart (Suis) – Circulation Support, Kali Carbonicum - Fatigue, Ranunculus Bulbosus – Circulation Support, Spigelia Anthelmia – Nighttime Restlessness, Sulphur - Fatigue

USES:

• For the temporary relief of symptoms including:

• circulation support • fatigue • nighttime restlessness

These statements are based upon homeopathic principles. They have not been reviewed by the Food and Drug Administration.

WARNINGS:

If pregnant or breast-feeding, ask a health professional before use.

Keep out of reach of children. In case of overdose, contact a physician or Poison Control Center right away.

Tamper Evident: Sealed for your protection. Do not use if seal is broken or missing.

KEEP OUT OF REACH OF CHILDREN:

In case of overdose, contact a physician or Poison Control Center right away.

DIRECTIONS:

1-10 drops under the tongue, 3 times a day or as directed by a health professional. Consult a physician for use in children under 12 years of age.

INACTIVE INGREDIENTS:

Demineralized water, 25% ethanol

QUESTIONS:

Dist. By: Deseret Biologicals, Inc.
469 W. Parkland Drive
Sandy, UT 84070

www.desbio.com

800-827-8204

PACKAGE LABEL DISPLAY:

Des Bio

Heart/Fatigue

Homeopathic
NDC 43742-1295-1
1 FL OZ (30 ml)